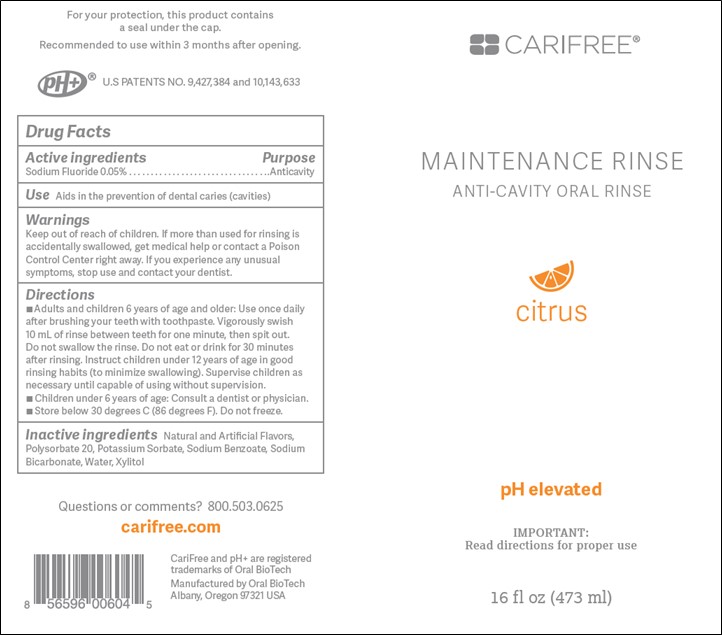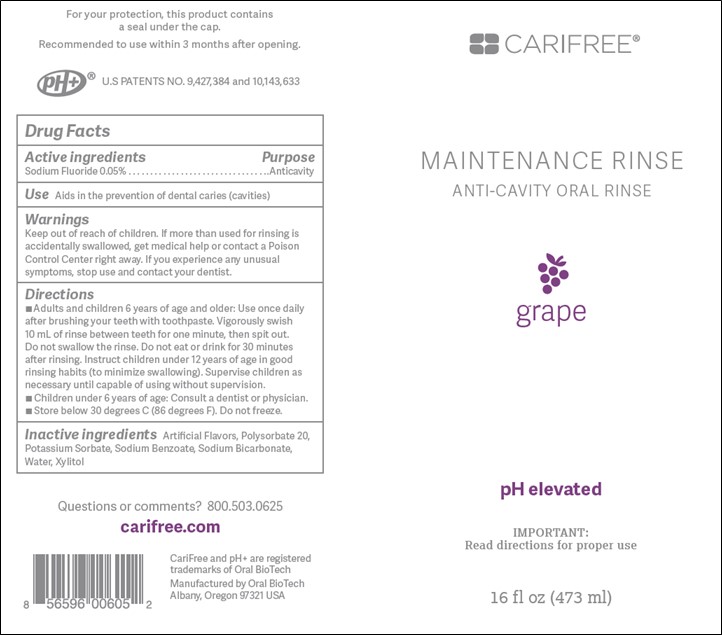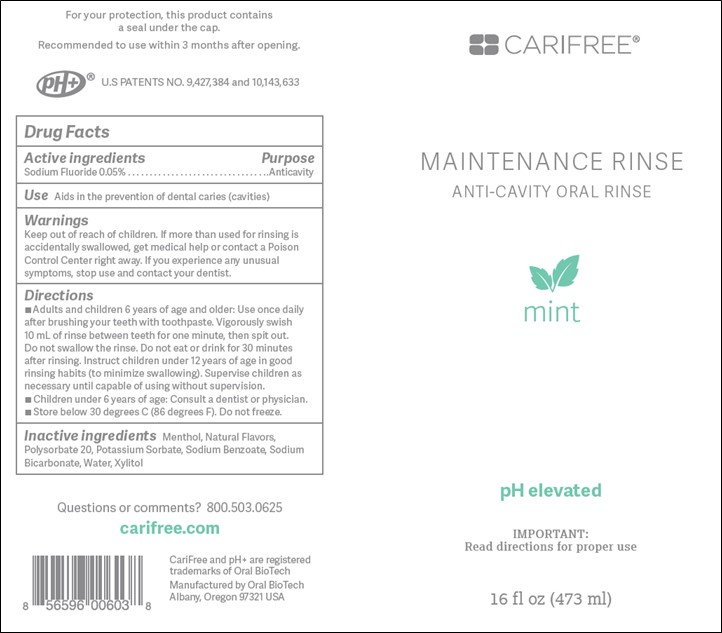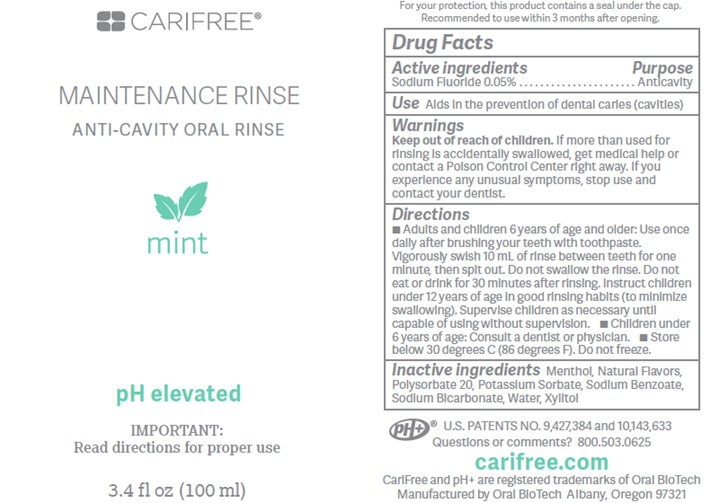 DRUG LABEL: Maintenance Rinse
NDC: 61578-313 | Form: RINSE
Manufacturer: Dental Alliance Holdings LLC
Category: otc | Type: HUMAN OTC DRUG LABEL
Date: 20240131

ACTIVE INGREDIENTS: SODIUM FLUORIDE 226 ug/1 mL
INACTIVE INGREDIENTS: POLYSORBATE 20; POTASSIUM SORBATE; SODIUM BENZOATE; SODIUM BICARBONATE; WATER; XYLITOL

Maintenance Rinse

Active ingredients:

Sodium Fluoride 0.05%

Purpose:

Anticavity

Use:

Aids in the prevention of dental caries (cavities)

Warnings:

Keep out of reach of children. If more than used for rinsing is accidentally swallowed, get medical help or contact a Poison Control Center right away. If you experience any unusual symptoms, stop use and contact your dentist.

Warnings:

Keep out of reach of children.

Directions:

Adults and children 6 years of age and older: Use once daily after brushing your teeth with toothpaste. Vigorously swish 10mL of rinse between teeth for one minute, then spit out. Do not swallow the rinse. Do not eat or drink for 30 minutes after rinsing. Instruct children under 12 years of age in good rinsing habits (to minimize swallowing). Supervise children as necessary until capable of using without supervision. Children under 6 years of age: Consult a dentist or physician. Store below 30 degrees C (86 degrees F). Do not freeze.

Inactive ingredients:

Menthol (Mint only), Natural Flavors (Mint only), Natural and Artificial Flavors (Citrus and Grape only), Polysorbate 20, Potassium Sorbate, Sodium Benzoate, Sodium Bicarbonate, Water, Xylitol